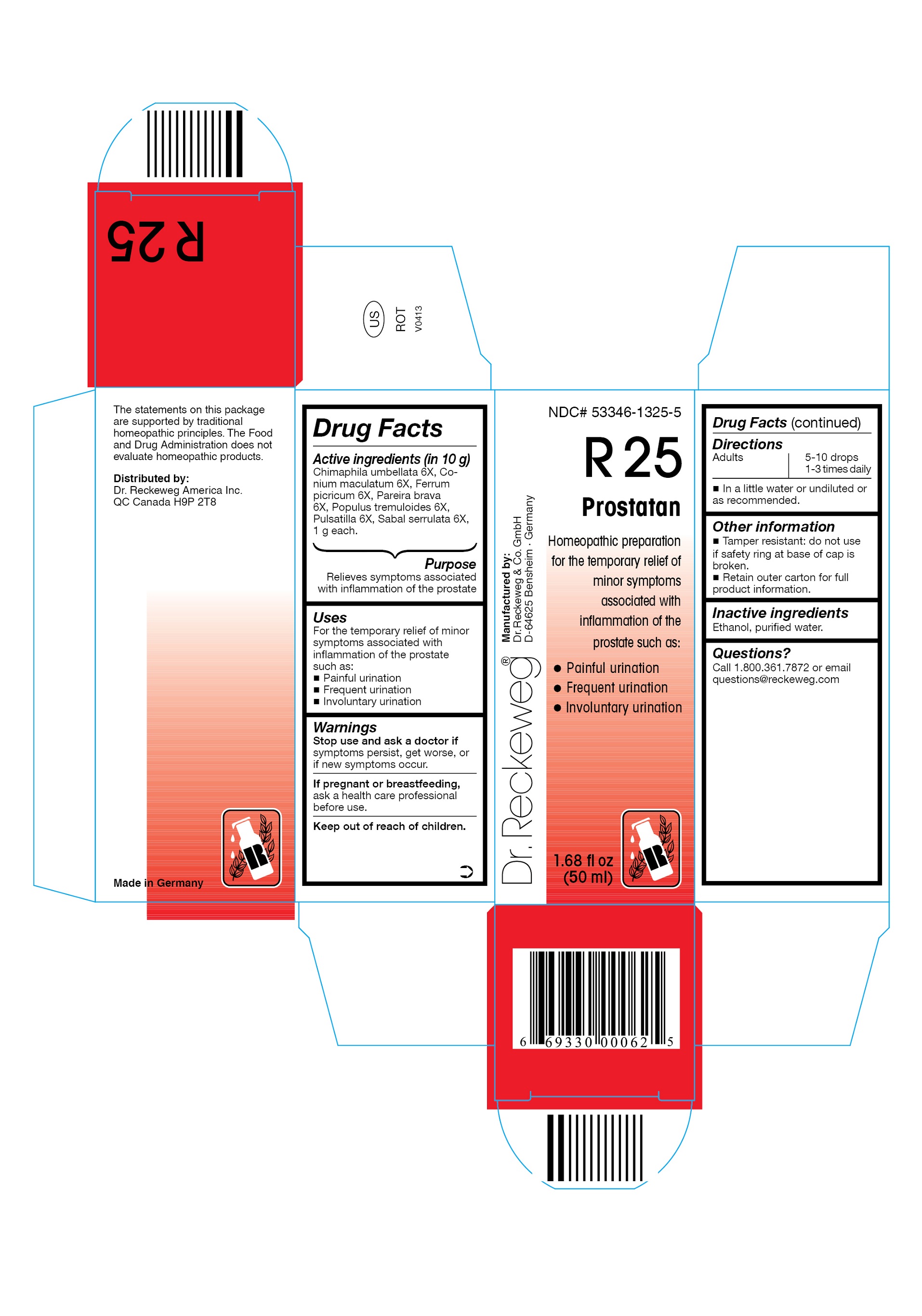 DRUG LABEL: DR. RECKEWEG R25 Prostatan
NDC: 53346-1325 | Form: LIQUID
Manufacturer: PHARMAZEUTISCHE FABRIK DR. RECKEWEG & CO
Category: homeopathic | Type: HUMAN OTC DRUG LABEL
Date: 20130404

ACTIVE INGREDIENTS: CHIMAPHILA UMBELLATA 6 [hp_X]/50 mL; CONIUM MACULATUM FLOWERING TOP 6 [hp_X]/50 mL; FERRIC PICRATE 6 [hp_X]/50 mL; CHONDRODENDRON TOMENTOSUM ROOT 6 [hp_X]/50 mL; POPULUS TREMULOIDES BARK 6 [hp_X]/50 mL; POPULUS TREMULOIDES LEAF 6 [hp_X]/50 mL; PULSATILLA PRATENSIS 6 [hp_X]/50 mL; SAW PALMETTO 6 [hp_X]/50 mL
INACTIVE INGREDIENTS: ALCOHOL; WATER

DR. RECKEWEG R25 Prostatan

Active ingredients

Chimaphila umbellata 6X, Conium maculatum 6X, Ferrum picricum 6X, Pareira brava 6X, Populus tremuloides 6X, Pulsatilla 6X, Sabal serrulata 6X, 1 g each in 10 g.

Purpose

Relieves symptoms associated with inflammation of the prostate

Uses

For the temporary relief of minor symptoms associated with inflammation of the prostate such as:

- Painful urination
- Frequent urination
- Involuntary urination

Warnings

Stop use and ask a doctor if symptoms persist, get worse, or if new symptoms occur.

PREGNANCY OR BREAST FEEDING

If pregnant or breastfeeding, ask a health care professional before use.

Keep out of reach of children.

Directions

Adults 5-10 drops 1-3 times daily in a little water or undiluted or as recommended.

Other information

- Tamper resistant: do not use if safety ring at base of cap is broken.
- Retain outer carton for full product information.

Inactive ingredients

Ethanol, purified water.

Questions?

Call 1-800-361-7872 or email questions@reckeweg.com

PACKAGE LABEL

NDC# 53346-1325-5

Dr. Reckeweg R25 Prostatan

Homeopathic preparation for the temporary relief of minor symptoms associated with inflammation of the prostate such as:

- Painful urination
- Frequent urination
- Involuntary urination

Manufactured by:

Dr. Reckeweg Co. GmbH

D-64625 Bensheim

Germany

1.68 fl oz
(50 ml)